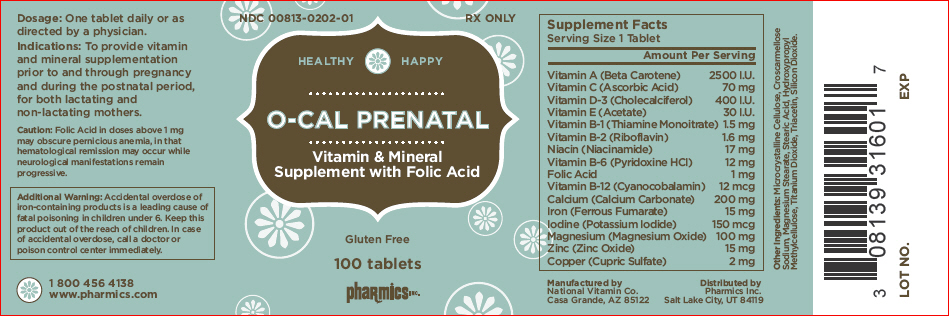 DRUG LABEL: O-Cal Prenatal Vitamin
NDC: 0813-0202 | Form: TABLET
Manufacturer: Pharmics, Inc.
Category: prescription | Type: HUMAN PRESCRIPTION DRUG LABEL
Date: 20120906

ACTIVE INGREDIENTS: Vitamin A 2500 [iU]/1 1; Ascorbic Acid 70 mg/1 1; Cholecalciferol 400 [iU]/1 1; .ALPHA.-TOCOPHEROL ACETATE 30 [iU]/1 1; THIAMINE MONONITRATE 1.5 mg/1 1; Riboflavin 1.6 mg/1 1; Niacin 17 mg/1 1; Pyridoxine 12 mg/1 1; Folic Acid 1 mg/1 1; Cyanocobalamin 12 ug/1 1; Calcium 200 mg/1 1; FERROUS FUMARATE 15 mg/1 1; Iodine 150 ug/1 1; Magnesium 100 mg/1 1; Zinc 15 mg/1 1; Copper 2 mg/1 1
INACTIVE INGREDIENTS: Cellulose, Microcrystalline; CROSCARMELLOSE SODIUM; Magnesium Stearate; Stearic Acid; Hypromelloses; Titanium Dioxide; Triacetin; Sodium Peroxide

O-CAL PRENATAL
Vitamin & Mineral
Supplement with Folic Acid

Supplement Facts Serving Size 1 Tablet
Amount Per Serving
Vitamin A (Beta Carotene) | 2500 I.U.
Vitamin C (Ascorbic Acid) | 70 mg
Vitamin D-3 (Cholecalciferol) | 400 I.U.
Vitamin E (Acetate) | 30 I.U.
Vitamin B-1 (Thiamine Monoitrate) | 1.5 mg
Vitamin B-2 (Riboflavin) | 1.6 mg
Niacin (Niacinamide) | 17 mg
Vitamin B-6 (Pyridoxine HCI) | 12 mg
Folic Acid | 1 mg
Vitamin B-12 (Cyanocobalamin) | 12 mcg
Calcium (Calcium Carbonate) | 200 mg
Iron (Ferrous Fumarate) | 15 mg
Iodine (Potassium Iodide) | 150 mcg
Magnesium (Magnesium Oxide) | 100 mg
Zinc (Zinc Oxide) | 15 mg
Copper (Cupric Sulfate) | 2 mg

Other Ingredients

Microcrystalline Cellulose, Croscarmellose Sodium, Magnesium Stearate, Stearic Acid, Hydroxypropyl Methylcellulose, Titanium Dioxide, Triacetin, Silicon Dioxide.

Dosage

One tablet daily or as directed by a physician.

Indications

To provide vitamin and mineral supplementation prior to and through pregnancy and during the postnatal period, for both lactating and non-lactating mothers.

Caution

Folic Acid in doses above 1 mg may obscure pernicious anemia, in that hematological remission may occur while neurological manifestations remain progressive.

Additional Warning

Accidental overdose of iron-containing products is a leading cause of fatal poisoning in children under 6. Keep this product out of the reach of children. In case of accidental overdose, call a doctor or poison control center immediately.

1 800 456 4138
www.pharmics.com

Manufactured by
National Vitamin Co.
Casa Grande, AZ 85122

Distributed by
Pharmics Inc.
Salt Lake City, UT 84119

PRINCIPAL DISPLAY PANEL - 100 Tablet Bottle Label

NDC 00813-0202-01

RX ONLY

HEALTHY
HAPPY

O-CAL PRENATAL

Vitamin & Mineral
Supplement with Folic Acid

Gluten Free

100 tablets

pharmics INC.